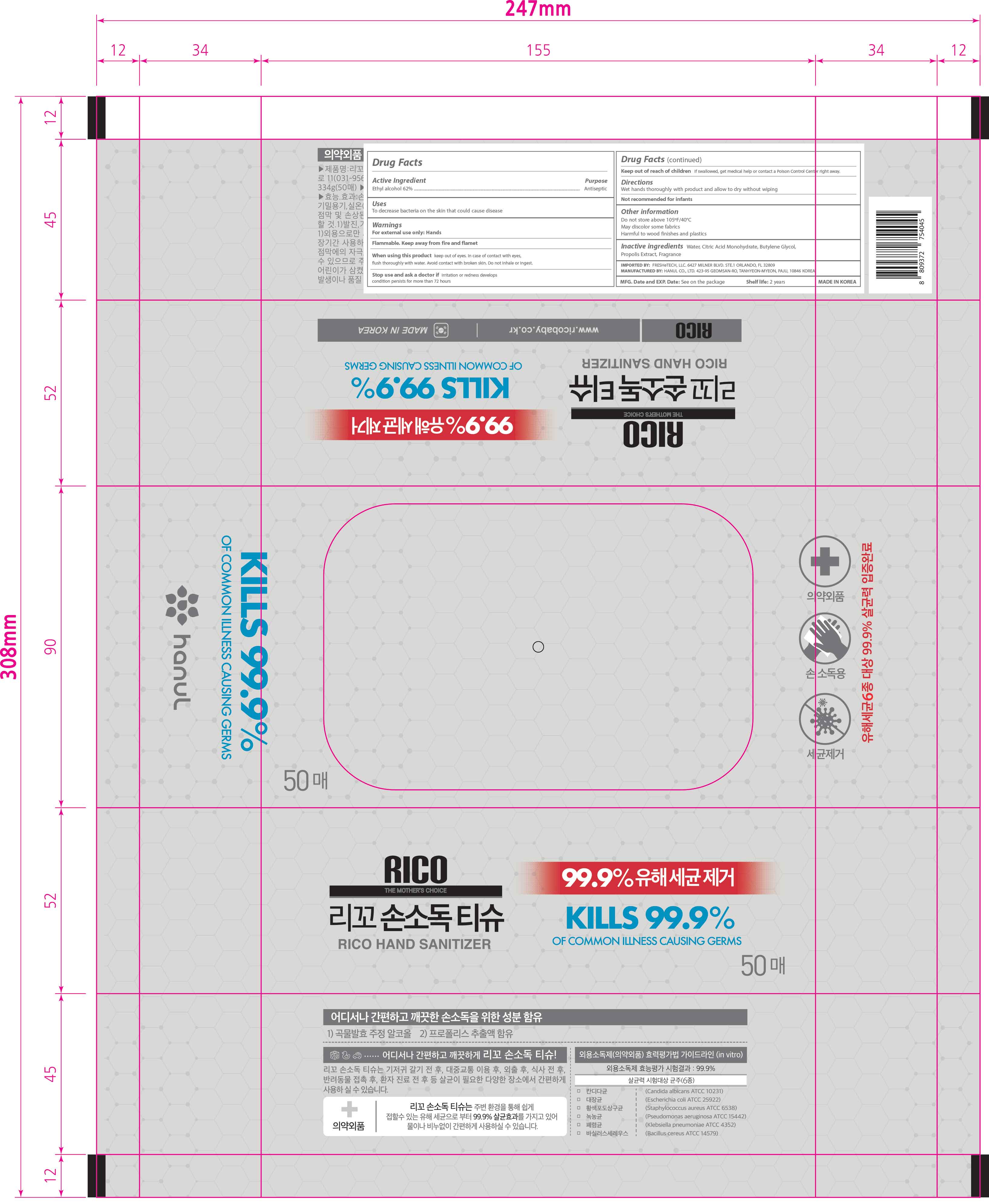 DRUG LABEL: Rico Hand Sanitizer
NDC: 75214-504 | Form: CLOTH
Manufacturer: HANUL CO.,LTD
Category: otc | Type: HUMAN OTC DRUG LABEL
Date: 20250120

ACTIVE INGREDIENTS: ALCOHOL 65.67 mL/100 mL
INACTIVE INGREDIENTS: ANHYDROUS CITRIC ACID 0.03 mL/100 mL; BUTYLENE GLYCOL 0.5 mL/100 mL; WATER 33.74 mL/100 mL; PROPOLIS WAX 0.01 mL/100 mL

Rico Hand Sanitizer Wipes 50

Active Ingredient(s)

Alcohol 62% v/v. Purpose: Antiseptic

Purpose

Antiseptic, Hand Sanitizer

Use

To decrease bacteria on the skin that could cause disease

Warnings

For external use only: Hands

Flammable. Keep away from fire and flame.

When using this product

keep out of eyes. In case of contact with eyes, flush thoroughly with water.

avoid contact with broken skin

do not inhale or ingest

Stop use and ask a doctor if

irritation or redness develops

condition persists for more than 72 hours

Keep out of reach of children. If swallowed, get medical help or contact a Poison Control Center right away.

Directions

Wet hands thoroughly with product and allow to dry without wiping

Not recommended for infants

Other information

Do not store above 105ºF/40°C

May discolor some fabrics

Harmful to wood finishes and plastics

Inactive ingredients

Water, Citric Acid Monohydrate, Butylene Glycol, Propolis Extract, Fragrance

Package Label - Principal Display Panel

Rico Hand Sanitizer

50 wipes

kills 99.9% of common illness causing Germs